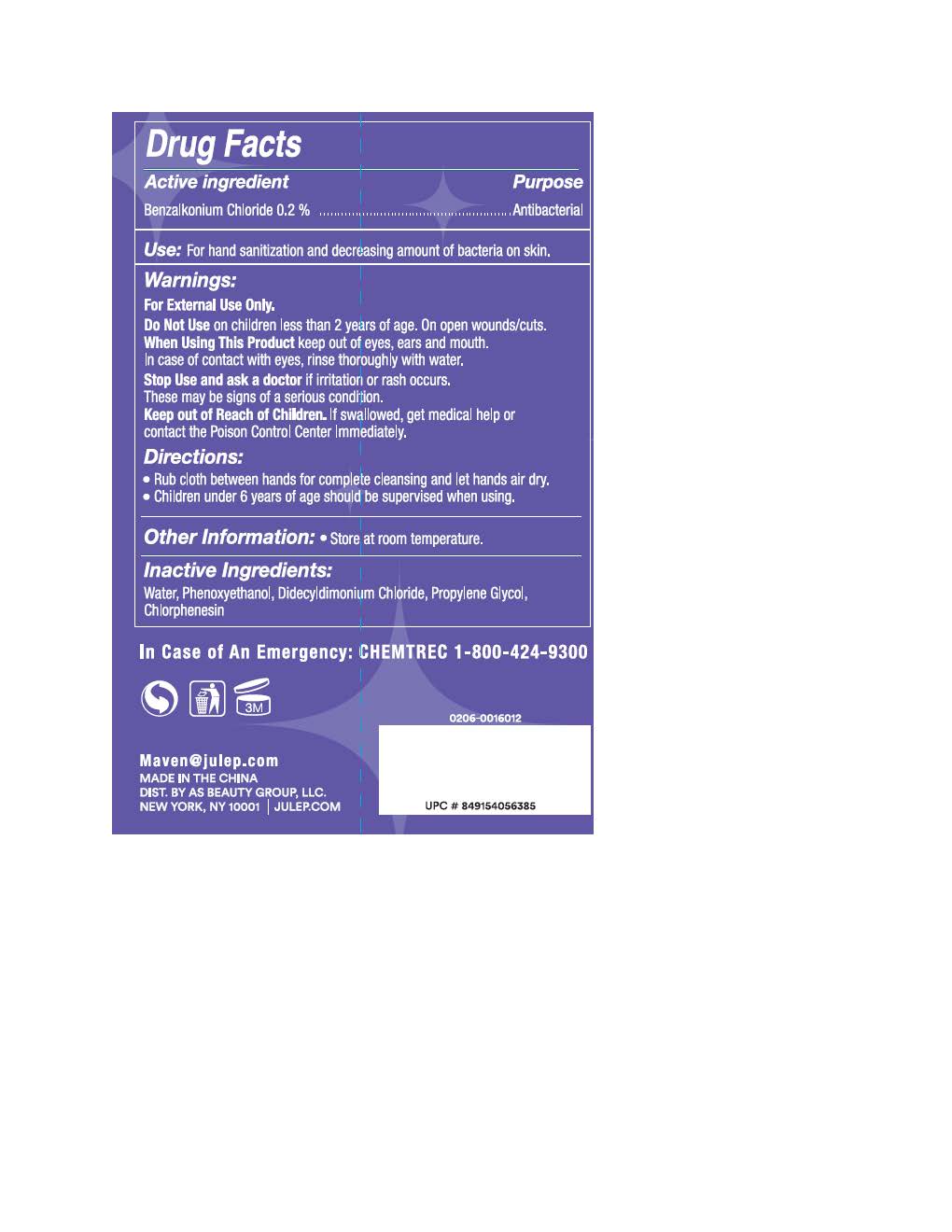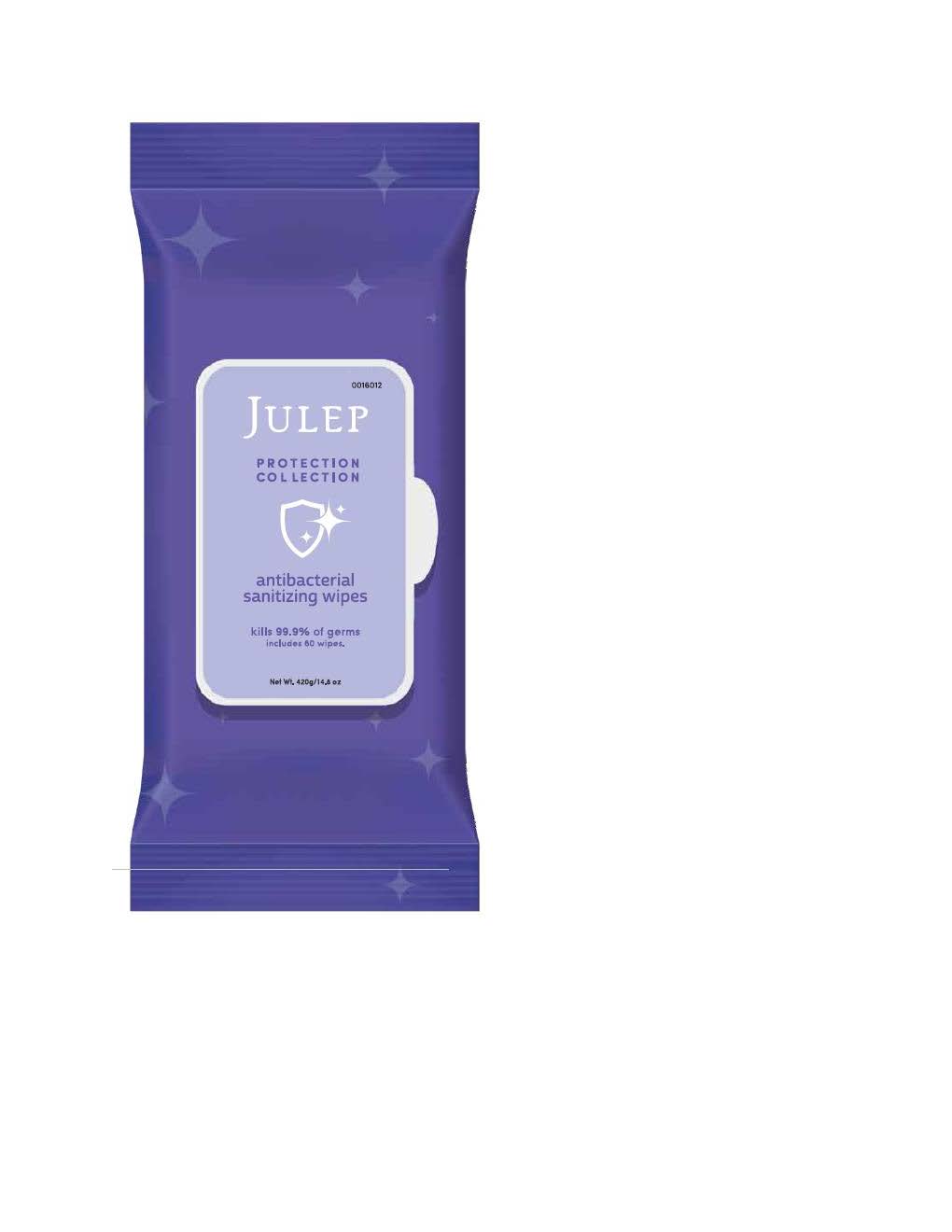 DRUG LABEL: Antibacterial Hand Wipes
NDC: 74884-120 | Form: CLOTH
Manufacturer: AS Beauty
Category: otc | Type: HUMAN OTC DRUG LABEL
Date: 20200519

ACTIVE INGREDIENTS: BENZALKONIUM CHLORIDE 0.2 g/0.2 g
INACTIVE INGREDIENTS: PHENOXYETHANOL; WATER; PROPYLENE GLYCOL; CHLORPHENESIN; DIDECYLDIMONIUM CHLORIDE

Usage

Rub cloth completely between hands and let air dry.

Non Active Ingredients

Water, Phenoxyethanol, Didecyldimonium Chloride, Propylene Glycol, Chlorphenesin.

Indications upon usage

Stop usage and consult a doctor if a rash or irritation occurs.

Not for Children

Keep away from Children

Product Purpose

Antibacterial

Warnings

For External Use Only.

Keep out of Eyes, Ears and Mouth.

Do not use on Open Wounds or Cuts